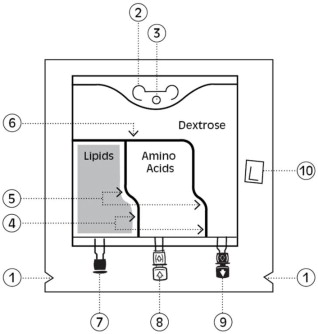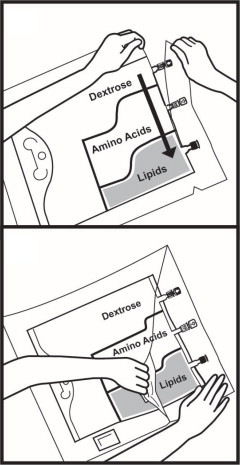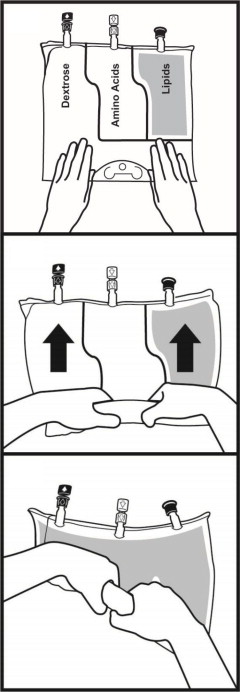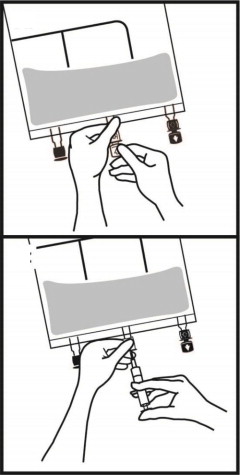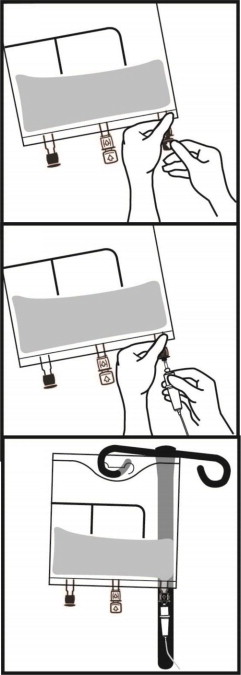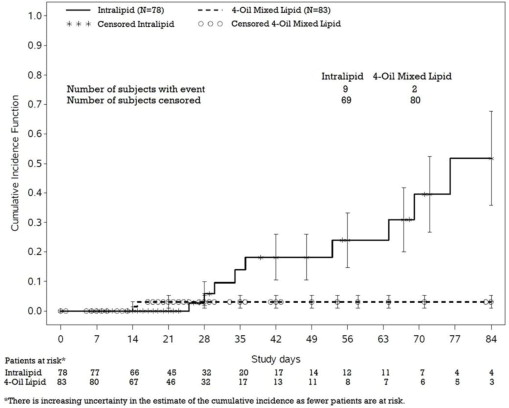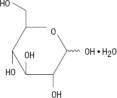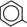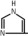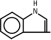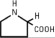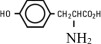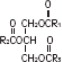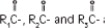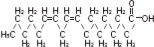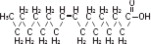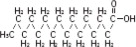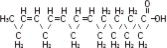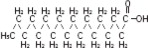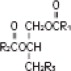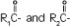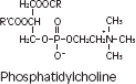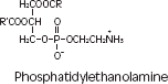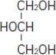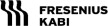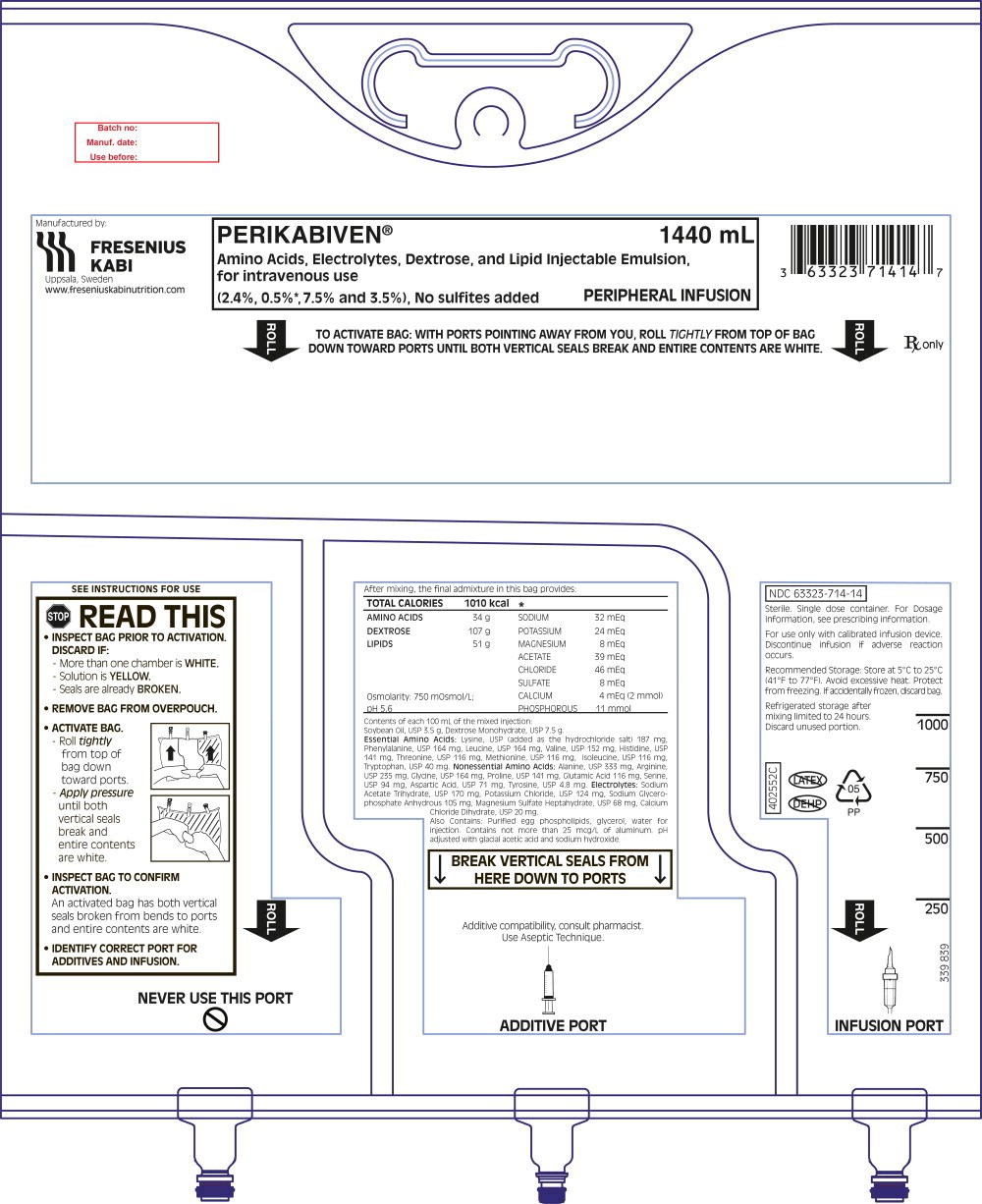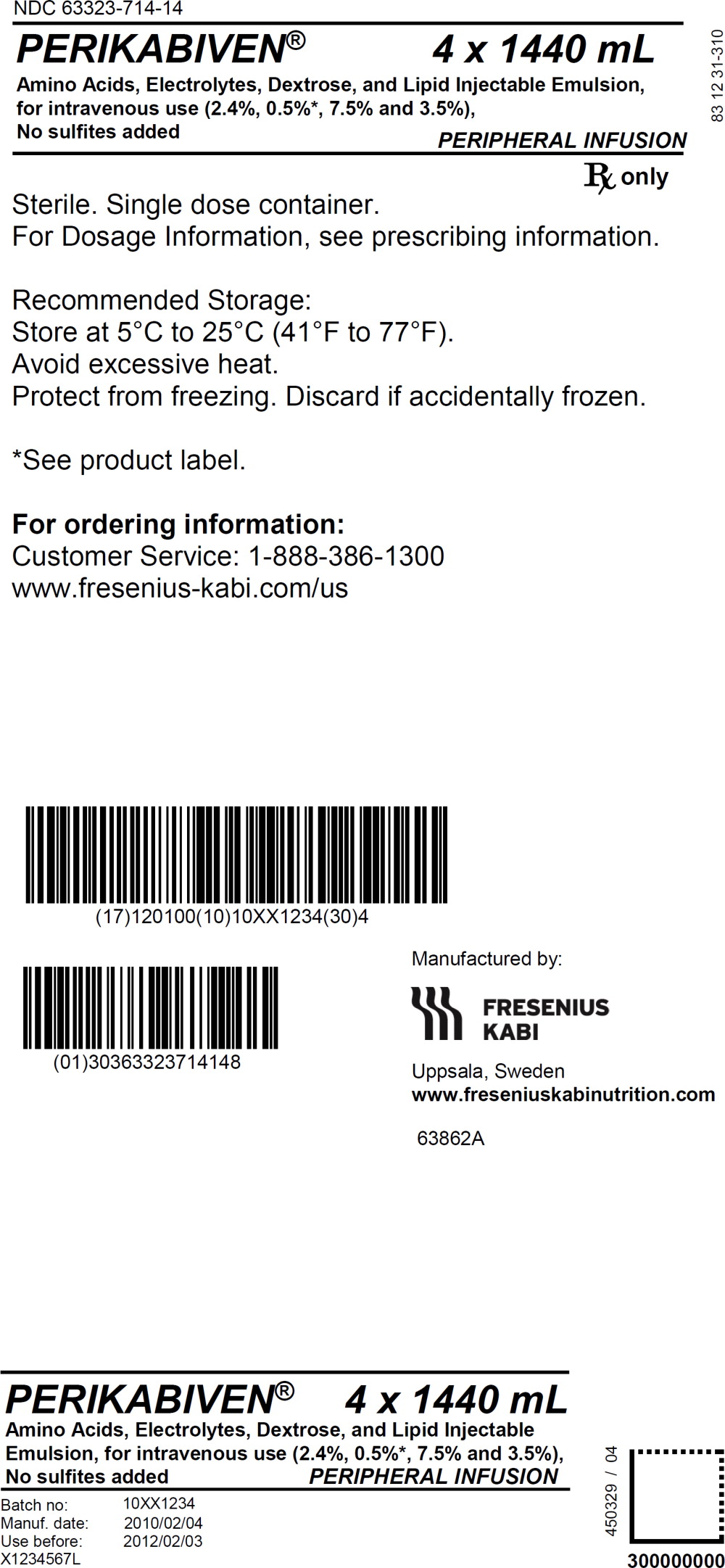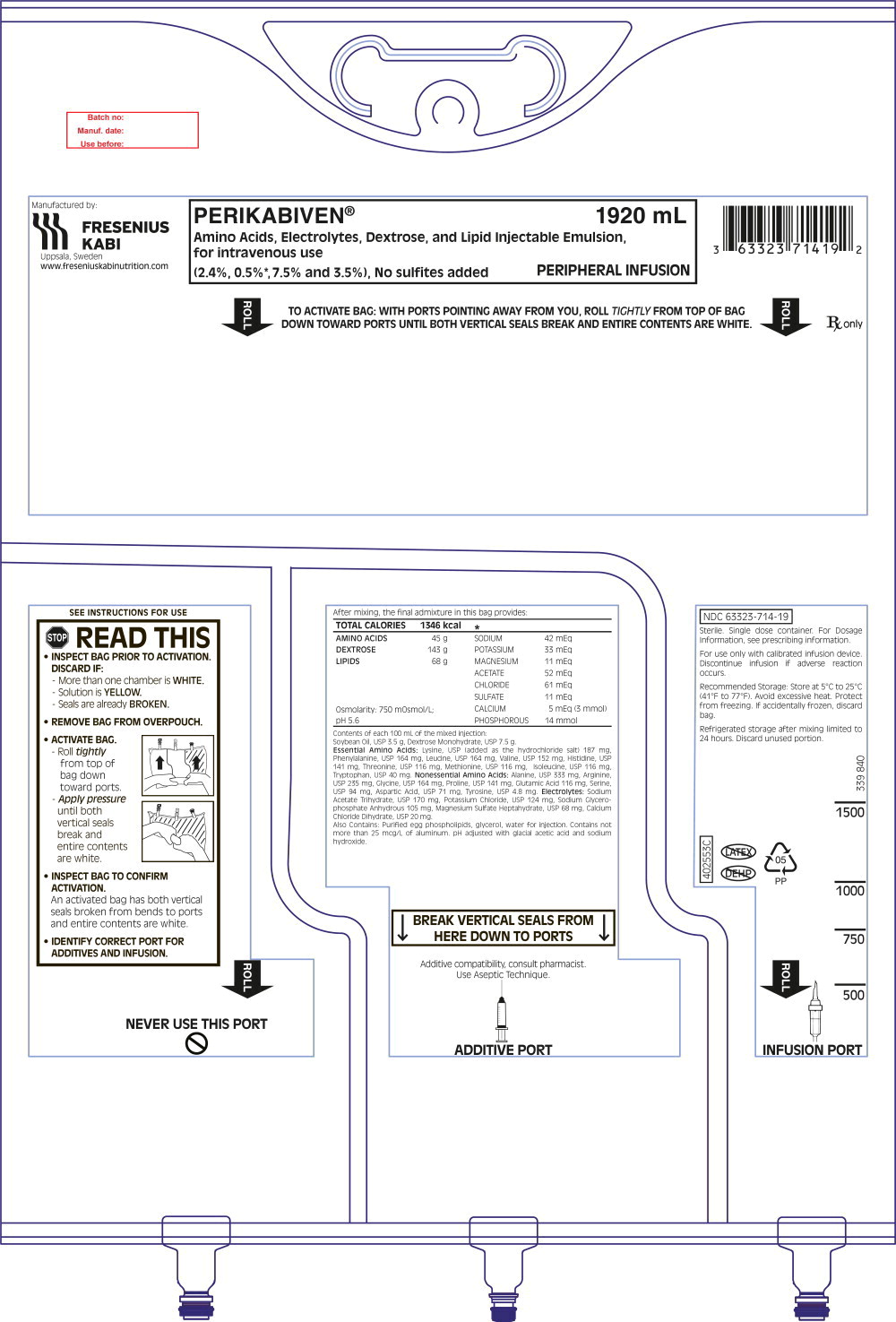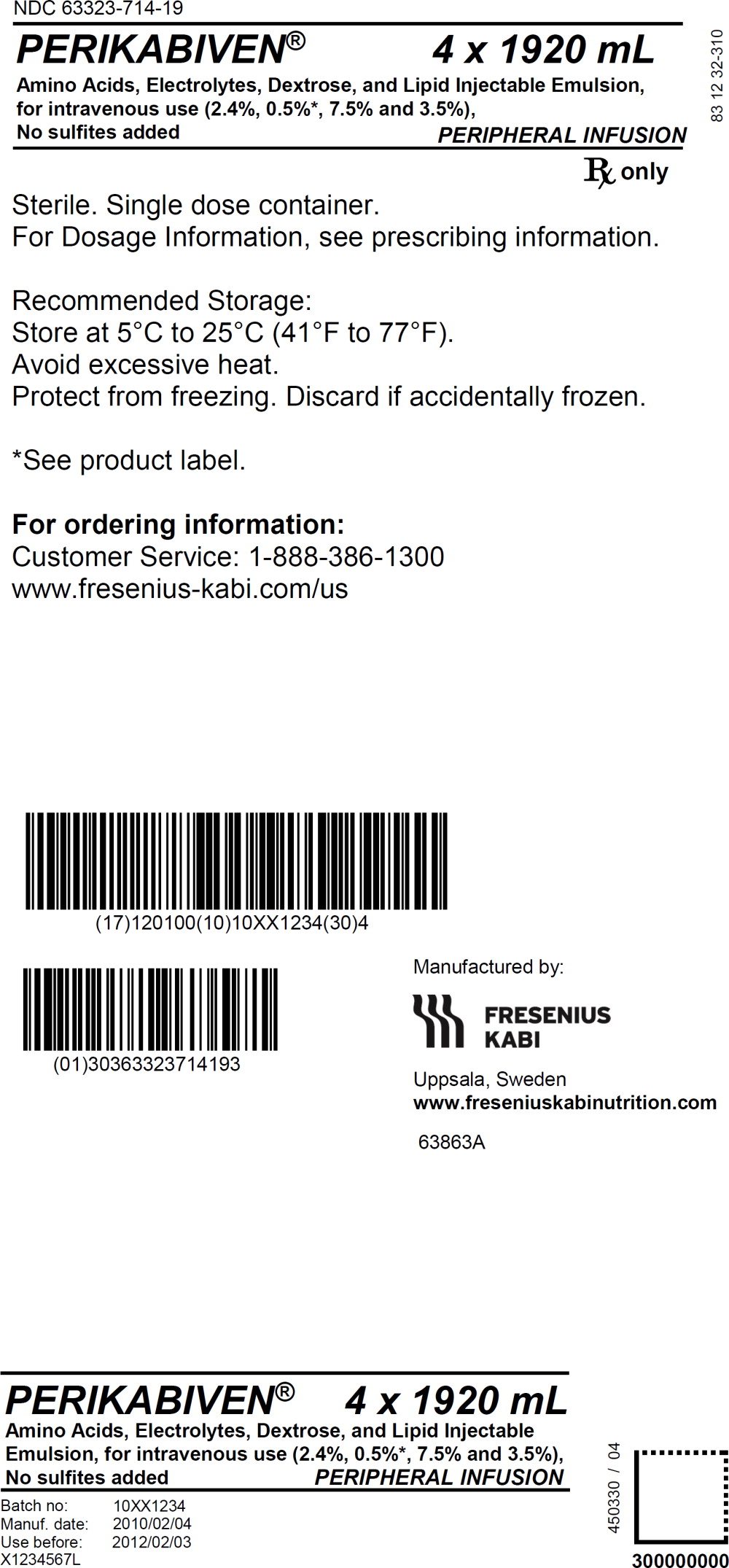 DRUG LABEL: Perikabiven
NDC: 63323-714 | Form: INJECTION, EMULSION
Manufacturer: Fresenius Kabi USA, LLC
Category: prescription | Type: HUMAN PRESCRIPTION DRUG LABEL
Date: 20250915

ACTIVE INGREDIENTS: DEXTROSE MONOHYDRATE 7.5 g/100 mL; SOYBEAN OIL 3.5 g/100 mL; SODIUM ACETATE 170 mg/100 mL; POTASSIUM CHLORIDE 124 mg/100 mL; SODIUM GLYCEROPHOSPHATE ANHYDROUS 105 mg/100 mL; MAGNESIUM SULFATE HEPTAHYDRATE 68 mg/100 mL; CALCIUM CHLORIDE 20 mg/100 mL; LYSINE HYDROCHLORIDE 187 mg/100 mL; PHENYLALANINE 164 mg/100 mL; LEUCINE 164 mg/100 mL; VALINE 152 mg/100 mL; HISTIDINE 141 mg/100 mL; THREONINE 116 mg/100 mL; METHIONINE 116 mg/100 mL; ISOLEUCINE 116 mg/100 mL; TRYPTOPHAN 40 mg/100 mL; ALANINE 333 mg/100 mL; ARGININE 235 mg/100 mL; GLYCINE 164 mg/100 mL; PROLINE 141 mg/100 mL; GLUTAMIC ACID 116 mg/100 mL; SERINE 94 mg/100 mL; ASPARTIC ACID 71 mg/100 mL; TYROSINE 4.8 mg/100 mL
INACTIVE INGREDIENTS: EGG PHOSPHOLIPIDS; GLYCERIN; WATER; SODIUM HYDROXIDE; ACETIC ACID

HIGHLIGHTS OF PRESCRIBING INFORMATION

These highlights do not include all the information needed to use PERIKABIVEN safely and effectively. See full prescribing information for PERIKABIVEN.
PERIKABIVEN® (amino acids, electrolytes, dextrose and lipid injectable emulsion), for intravenous use
Initial U.S. Approval: 2014

RECENT MAJOR CHANGES

Warnings and Precautions (5.4) | 7/2025

1 INDICATIONS AND USAGE

PERIKABIVEN is indicated as a source of calories, protein, electrolytes and essential fatty acids for adult patients requiring parenteral nutrition when oral or enteral nutrition is not possible, insufficient, or contraindicated.

PERIKABIVEN may be used to prevent essential fatty acid deficiency or treat negative nitrogen balance in adult patients. (1)

Limitations of Use:

Not recommended for use in pediatric patients <2 years including preterm infants because the fixed content of the formulation does not meet nutritional requirements in this age group. (1, 5.1, 8.4)

2 DOSAGE AND ADMINISTRATION

- For intravenous infusion into a peripheral or central vein. (2.1, 5.11)
- See full prescribing information regarding preparation, administration, instructions for use, the recommended dosage in adults, and dosage modifications for patients with renal impairment. (2.1, 2.2, 2.3, 2.4)

3 DOSAGE FORMS AND STRENGTHS

- PERIKABIVEN is a sterile, hypertonic emulsion in a three chamber container. The individual chambers contain one of the following respectively: amino acids and electrolytes, dextrose, or lipid injectable emulsion. (3)
- PERIKABIVEN is available in two sizes 1,920 mL and 1,440 mL. (3)

4 CONTRAINDICATIONS

- Concomitant treatment with ceftriaxone in neonates (28 days of age or younger). (4)
- Known hypersensitivity to egg, soybean, peanut or any of the active ingredients or excipients. (4)
- Severe disorders of lipid metabolism characterized by hypertriglyceridemia (serum triglycerides >1,000 mg/dL). (4, 5.10)
- Inborn errors of amino acid metabolism. (4)
- Cardiopulmonary instability. (4)
- Hemophagocytic syndrome. (4)

5 WARNINGS AND PRECAUTIONS

- Clinical Decompensation with Rapid Infusion of Intravenous Lipid Emulsion in Neonates and Infants: Acute respiratory distress, metabolic acidosis, and death after rapid infusion of intravenous lipid emulsions have been reported. (5.1)
- Parenteral Nutrition-Associated Liver Disease: Increased risk in patients who receive parenteral nutrition for greater than 2 weeks. Monitor liver tests; if abnormalities occur, consider discontinuation or dosage reduction. (5.2)
- Pulmonary Embolism and Respiratory Distress due to Pulmonary Vascular Precipitates: If signs of pulmonary distress occur, stop the infusion and initiate a medical evaluation. (5.3)
- Hypersensitivity Reactions: Monitor for signs or symptoms and discontinue infusion if reactions occur. (5.4)
- Precipitation with Ceftriaxone: Do not administer ceftriaxone simultaneously with PERIKABIVEN via a Y-Site (4, 5.5, 8.4)
- Infection, fat overload, hyperglycemia and refeeding complications: Monitor for signs and symptoms; monitor laboratory parameters. (5.6, 5.7, 5.8, 5.9, 5.14)

6 ADVERSE REACTIONS

The most common adverse reactions (≥3%) are hyperglycemia, hypokalemia, pyrexia, and increased blood triglycerides. (6.1)

To report SUSPECTED ADVERSE REACTIONS, contact Fresenius Kabi USA, LLC at 1-800-551-7176 or FDA at 1-800-FDA-1088 or www.fda.gov/medwatch.

7 DRUG INTERACTIONS

Coumarin and coumarin derivatives, including warfarin: Anticoagulant activity may be counteracted; monitor laboratory parameters. (7.1)

FULL PRESCRIBING INFORMATION

1 INDICATIONS AND USAGE

PERIKABIVEN is indicated as a source of calories, protein, electrolytes and essential fatty acids for adult patients requiring parenteral nutrition when oral or enteral nutrition is not possible, insufficient, or contraindicated. PERIKABIVEN may be used to prevent essential fatty acid deficiency or treat negative nitrogen balance in adult patients.

Limitations of Use:

PERIKABIVEN is not recommended for use in pediatric patients under the age of 2 years, including preterm infants because the fixed content of the formulation does not meet the nutritional requirements of this age group [see Warnings and Precautions (5.1) and Use in Specific Populations (8.4)].

2 DOSAGE AND ADMINISTRATION

2.1 Administration

- PERIKABIVEN is for intravenous infusion into a peripheral or central vein [see Warnings and Precautions (5.11)].
- Use a 1.2 micron in-line filter.
- Use of a vented intravenous administration set with the vent in the open position could result in air embolism.
- Use a dedicated line without any connections. Multiple connections could result in air embolism due to residual air being drawn from the primary container before administration of the fluid from the secondary container is completed.
- Do not exceed the recommended maximum infusion rate of 3.7 mL/kg/hour [see Dosage and Administration (2.4) and Warnings and Precautions (5.1)].
- Ceftriaxone must not be administered simultaneously with calcium-containing intravenous solutions such as PERIKABIVEN via a Y-site due to precipitation. However, in patients other than neonates, ceftriaxone and PERIKABIVEN may be administered sequentially if the infusion lines are thoroughly flushed between infusions with a compatible fluid [see Contraindications (4), Warnings and Precautions (5.5)].
- Do not use administration sets and lines that contain di-2-ethylhexyl phthalate (DEHP). Administration sets that contain polyvinyl chloride (PVC) components have DEHP as a plasticizer.

2.2 Important Preparation Instructions

- Inspect the bag prior to activation. Discard the bag in the following situations:
  ͦ Evidence of damage to the bag
  ͦ More than one chamber is white
  ͦ Solution is yellow
  ͦ Any seal is already broken
- Activate the bag [see Dosage and Administration (2.3)].
- Once the bag is activated, ensure the vertical seals between chambers are broken at least from the bend in the seals and down to the ports. The upper sections of the vertical seals above the bend and the horizontal seal may remain closed.
- It is recommended to mix the contents thoroughly by inverting the bag upside down to ensure a homogenous admixture.
- Ensure the vertical seals between chambers are broken and the contents of all three chambers are mixed together prior to infusion [see Dosage and Administration (2.3)].
- Use PERIKABIVEN immediately after mixing and the introduction of additives. If not used immediately, the storage time and conditions prior to use should not be longer than 24 hours at 2° to 8°C (36° to 46°F). After removal from storage at 2° to 8°C (36° to 46°F), the admixture should be infused within 24 hours. Any mixture remaining must be discarded.
- For total parenteral nutrition add multivitamins and trace elements via the additive port. Any other additions to the bag should be evaluated by a pharmacist for compatibility. Questions about compatibility may be directed to Fresenius Kabi USA, LLC.
- When introducing additives, it is recommended to use 18 to 23 gauge needles with a maximum length of 1.5 inches (40 mm) and to mix thoroughly after each addition, use aseptic technique and add after the vertical seals have been broken (i.e., bag has been activated) and the three components are mixed [see Dosage and Administration (2.3)].
- Parenteral drug products should be inspected visually for particulate matter and discoloration prior to administration, whenever solution and container permit. Inspect PERIKABIVEN to ensure:
  ͦ Precipitates have not formed during the mixing or addition of additives.
  ͦ The emulsion has not separated. Separation of the emulsion can be visibly identified by a yellowish streaking or the accumulation of yellowish droplets in the mixed emulsion.
Discard the admixture if any of the above are observed.

2.3 Instructions for Use

1. Overpouch Notch
2. Handle
3. Hole (For hanging the bag)
4. Vertical Seals (Must break to activate)
5. Bends in Vertical Seals
6. Horizontal Seal (May remain unopened)
7. Blind Port (NEVER use this port)
8. WHITE Additive Port
9. BLUE Infusion Port
10. Oxygen Absorber (Present between bag and inside overpouch-position may vary)
An instructional video is available at www.freseniuskabinutrition.com/products/kabiv en-perikabiven/.

1. INSPECT BAG PRIOR TO ACTIVATION.

- PERIKABIVEN is a 3 chambered bag:
  - One chamber is WHITE.
  - Two chambers are CLEAR.
  a) Discard bag if:
  - Overpouch is OPENED OR DAMAGED.
  - More than one chamber is WHITE.
  - Solution is YELLOW.
  - Seals are already BROKEN.

2. REMOVE OVERPOUCH.

a) Place bag on a clean, flat surface.
b) Tear from Overpouch Notch, located close to the ports.
c) Tear long sides open to access the inner bag.
d) Discard Overpouch and Oxygen Absorber.

3. ACTIVATE BAG.

a) Place bag on a clean, flat surface with text side up and ports pointing away from you.
b) Roll tightly from top of bag down toward ports.
c) Apply pressure until both Vertical Seals break and entire contents are white. It may take up to 5 seconds of continued pressure to break Vertical Seals.

NOTE: Both Vertical Seals must be broken from bends to ports. Upper section of Vertical Seals and Horizontal Seal may remain unbroken.

d) After both Vertical Seals are broken, mix contents thoroughly by inverting the bag at least three times to ensure a homogenous mixture.

4. INSPECT BAG TO CONFIRM ACTIVATION.

- An activated bag has both Vertical Seals broken from bends to ports and entire contents are white.

5. IDENTIFY CORRECT PORT.

- Additive port is WHITE with arrow pointing toward bag.
- Infusion port is BLUE with arrow pointing away from bag.

6. MAKE ADDITIONS (if prescribed). WARNING: Ensure additives are compatible.

a) Immediately before injecting additives, break off WHITE Additive Port cap with the arrow pointing toward the bag.
b) Hold base of Additive Port horizontally.
c) Insert needle horizontally through the center of Additive Port's septum and inject additives.
d) Repeat as necessary using aseptic technique.
e) Mix thoroughly after each addition.

NOTE: The membrane of Additive Port is sterile at first use. Use aseptic technique for subsequent additions. The septum can be pierced up to 10 times with the recommended needle size 18 to 23 G 1½ inches (40mm).

7. SPIKE AND HANG BAG.

a) Immediately before inserting the infusion set, break off BLUE Infusion Port cap with the arrow pointing away from the bag.
b) Use a non-vented infusion set or close the air- inlet on a vented set. It is recommended to use 1.2 μm in-line filter.
c) Close the roller clamp of the infusion set.
d) Hold the base of Infusion Port.
e) Insert spike through Infusion Port by rotating your wrist slightly until the spike is inserted.
f) Lift and hold the bag with both hands.
g) Hang the bag by Hole below Handle.

NOTE: The membrane of Infusion Port is sterile at first use. Use infusion sets (according to ISO Number 8536-4) with an external spike diameter of 5.5 to 5.7 mm.

8. FOR SINGLE USE ONLY.

- Discard unused portion.

2.4 Dosing Considerations

The dosage of PERIKABIVEN should be individualized based on the patient's clinical condition (ability to adequately metabolize amino acids, dextrose and lipids), body weight and nutritional/fluid requirements, as well as additional energy given orally/enterally to the patient.

PERIKABIVEN is a combination of amino acids, electrolytes, dextrose, and lipids in a fixed volume and concentration. The dosage selection is based upon fluid requirements which can be used in conjunction with the nutritional requirements to determine final dosage [see Table 1].

PERIKABIVEN meets the total nutritional requirements for protein, dextrose and lipids in stable patients, and can be individualized to meet specific needs with the addition of nutrients. The maximum infusion rate is based upon the dextrose component.

Prior to administration of PERIKABIVEN, correct severe fluid, electrolyte and acid-base disorders. Before starting the infusion, obtain serum triglyceride levels to establish the baseline value.

Recommended Adult Dosage

The recommended dosage of PERIKABIVEN in adults is 27 to 40 mL/kg/day. The amount of macronutrients provided by PERIKABIVEN are shown in Table 1.

The maximum daily dosage of PERIKABIVEN in adults should not exceed 40 mL/kg/day.

In patients with serum triglyceride concentrations above 400 mg/dL, stop the PERIKABIVEN infusion and monitor serum triglyceride levels. Once the triglycerides are <400 mg/dL, restart PERIKABIVEN at a lower infusion rate and advance rate in smaller increments towards target dosage, checking the triglyceride levels prior to each adjustment [see Contraindications (4) and Warnings and Precautions (5.13)].

Table 1: Macronutrient Content of PERIKABIVEN Based on Recommended Dosage
 | Nutrition Provided by PERIKABIVEN recommended dosage
Fluid mL/kg/day | 27 to 40
Protein* g/kg/day Nitrogen g/kg/day | 0.64 to 0.94 0.1 to 0.15
Dextrose ** g/kg/day | 2.03 to 3
Lipids g/kg/day | 0.95 to 1.4
Total Energy Requirement kcal/kg/day | 18 to 27
* Protein is provided as amino acids. When infused intravenously amino acids are metabolized and utilized as the building blocks of protein.
** As Dextrose monohydrate

Treatment with PERIKABIVEN may be continued for as long as is required by the patient's condition.

Dosing in Renal Impairment

In patients with renal impairment, the dosage of PERIKABIVEN should be the recommended adult dosage (see above). Prior to administration, correct severe fluid or electrolyte imbalances. Closely monitor serum electrolyte levels and adjust the volume of PERIKABIVEN administered as required [see Warnings and Precautions (5.12)].

Renal patients not needing dialysis require 0.6 to 0.8 g of protein/kg/day. Patients on dialysis or continuous renal replacement therapy should receive 1.2 to 1.8 g of protein/kg/day up to a maximum of 2.5 g of protein/kg/day based on nutritional status and estimated protein losses. The PERIKABIVEN dosage can be adjusted based on the treatment for the renal impairment, supplementing protein as indicated. Additional protein may be added to PERIKABIVEN bag or infused separately. If required, additional amino acids may be added to the PERIKABIVEN bag or infused separately.

Infusion Duration and Rate

The recommended duration of infusion for PERIKABIVEN is between 12 and 24 hours, depending on the clinical situation.

The maximum infusion rate of PERIKABIVEN is 3.7 mL/kg/hour. This corresponds to 0.09 g/kg/hour of amino acids, 0.28 g/kg/hour of dextrose (the rate limiting factor) and 0.13 g/kg/hour of lipids.

Dosing Instructions

1. Determine the fluid requirements (27 to 40 mL/kg/day) and the patient's nutritional requirements to be delivered, then select the corresponding PERIKABIVEN bag.
2. Determine the preferred duration of infusion (12 to 24 hours).
3. Ensure that the rate of infusion (PERIKABIVEN dosage in mL/kg/day divided by the preferred duration of infusion (hours)) does not exceed the maximum infusion rate for the patient (i.e., 3.7 mL/kg/hour). The infusion rate may need to be reduced and duration of infusion increased in order not to exceed the maximum infusion rate.
4. Once the infusion rate in mL/kg/hour has been selected, calculate the infusion rate (mL/hour) using the patient's weight.
5. Compare the patient's nutrient requirements with the amount supplied by PERIKABIVEN. Discuss with a pharmacist any additions that may be required.

3 DOSAGE FORMS AND STRENGTHS

PERIKABIVEN is a sterile, hypertonic emulsion in a three chamber container. The individual chambers contain one of the following respectively: amino acids and electrolytes, dextrose, or lipid injectable emulsion. Table 2 describes the individual components of PERIKABIVEN.

Table 2: Contents of PERIKABIVEN when mixed
How Supplied | 1,440 mL | 1,920 mL
Composition of PERIKABIVEN
Soybean Oil, USP (g/100 mL) |  |  | 3.5
Dextrose Monohydrate, USP (g/100 mL) |  |  | 7.5
Amino Acids, USP (g/100 mL) |  |  | 2.36
Total Nitrogen (mg/100 mL) |  |  | 375
Essential amino acids (mg/100 mL) | Lysine, USP (added as the hydrochloride salt) |  | 187
Essential amino acids (mg/100 mL) | Phenylalanine, USP |  | 164
Essential amino acids (mg/100 mL) | Leucine, USP |  | 164
Essential amino acids (mg/100 mL) | Valine, USP |  | 152
Essential amino acids (mg/100 mL) | Histidine, USP |  | 141
Essential amino acids (mg/100 mL) | Threonine, USP |  | 116
Essential amino acids (mg/100 mL) | Methionine, USP |  | 116
Essential amino acids (mg/100 mL) | Isoleucine, USP |  | 116
Essential amino acids (mg/100 mL) | Tryptophan, USP |  | 40
Nonessential amino acids (mg/100 mL) | Alanine, USP |  | 333
Nonessential amino acids (mg/100 mL) | Arginine, USP |  | 235
Nonessential amino acids (mg/100 mL) | Glycine, USP |  | 164
Nonessential amino acids (mg/100 mL) | Proline, USP |  | 141
Nonessential amino acids (mg/100 mL) | Glutamic Acid |  | 116
Nonessential amino acids (mg/100 mL) | Serine, USP |  | 94
Nonessential amino acids (mg/100 mL) | Aspartic Acid, USP |  | 71
Nonessential amino acids (mg/100 mL) | Tyrosine, USP |  | 4.8
Electrolytes (mg/100 mL) | Sodium Acetate Trihydrate, USP |  | 170
Electrolytes (mg/100 mL) | Potassium Chloride, USP |  | 124
Electrolytes (mg/100 mL) | Sodium Glycerophosphate Anhydrous |  | 105
Electrolytes (mg/100 mL) | Magnesium Sulfate Heptahydrate, USP |  | 68
Electrolytes (mg/100 mL) | Calcium Chloride Dihydrate, USP |  | 20
Electrolyte Profile^1 (mEq/L) | Sodium^2 |  | 22 (22 mmol/L)
Electrolyte Profile^1 (mEq/L) | Potassium |  | 17 (17 mmol/L)
Electrolyte Profile^1 (mEq/L) | Magnesium |  | 5.6 (2.8 mmol/L)
Electrolyte Profile^1 (mEq/L) | Calcium |  | 2.8 (1.4 mmol/L)
Electrolyte Profile^1 (mEq/L) | Phosphorous^3 |  | N.A. (7.5 mmol/L)
Electrolyte Profile^1 (mEq/L) | Acetate^4 |  | 27 (27 mmol/L)
Electrolyte Profile^1 (mEq/L) | Chloride^5 |  | 32 (32 mmol/L)
Electrolyte Profile^1 (mEq/L) | Sulfate^6 |  | 5.6 (2.8 mmol/L)
Calorie Content (kcal/L) | From Dextrose^9 |  | 255
Calorie Content (kcal/L) | From Lipid |  | 350^7
Calorie Content (kcal/L) | From Amino Acids |  | 95
Calorie Content (kcal/L) | Total |  | 700
pH^8 |  |  | 5.6
Osmolarity (mOsm/L) |  |  | 750
1. Balanced by ions from amino acids
2. Contributed by sodium glycerophosphate and sodium acetate
3. Contributed by sodium glycerophosphate and phospholipids
4. Derived from sodium acetate and glacial acetic acid (for pH adjustment)
5. Contributed by calcium chloride, lysine hydrochloride, and potassium chloride
6. Derived from magnesium sulfate
7. Total caloric value including lipid, phospholipid and glycerin
8. pH of amino acid with electrolyte solution was adjusted with glacial acetic acid, USP and pH of lipid emulsion was adjusted with sodium hydroxide, USP
9. Calculated on the basis of 3.4 kcal/g of dextrose, monohydrate

4 CONTRAINDICATIONS

The use of PERIKABIVEN is contraindicated in:

- Neonates (28 days of age or younger) receiving concomitant treatment with ceftriaxone, even if separate infusion lines are used, due to the risk of fatal ceftriaxone calcium salt precipitation in the neonate's bloodstream [see Limitations of Use (1), Warnings and Precautions (5.5), Use in Specific Populations (8.4)].
- Patients with known hypersensitivity to egg, soybean, peanut or any of the active or inactive ingredients in PERIKABIVEN [see Warnings and Precautions (5.4)];
- Patients with severe disorders of lipid metabolism characterized by hypertriglyceridemia (serum triglyceride concentration >1,000 mg/dL) [see Warnings and Precautions (5.10)].
- Patients with inborn errors of amino acid metabolism
- Patients with cardiopulmonary instability (including pulmonary edema, cardiac insufficiency, myocardial infarction, acidosis and hemodynamic instability requiring significant vasopressor support)
- Patients with hemophagocytic syndrome

5 WARNINGS AND PRECAUTIONS

5.1 Clinical Decompensation with Rapid Infusion of Intravenous Lipid Emulsion in Neonates and Infants

In the postmarketing setting, serious adverse reactions including acute respiratory distress, metabolic acidosis, and death have been reported in neonates and infants after rapid infusion of intravenous lipid emulsions. Hypertriglyceridemia was commonly reported.

Preterm and small for gestational age infants have poor clearance of intravenous lipid emulsion and increased free fatty acid plasma levels following lipid emulsion infusion.

5.2 Parenteral Nutrition-Associated Liver Disease and Other Hepatobiliary Disorders

Risk of Parenteral Nutrition-Associated Liver Disease

Parenteral nutrition-associated liver disease (PNALD), also referred to as intestinal failure-associated liver disease (IFALD), can present as cholestasis or hepatic steatosis, and may progress to steatohepatitis with fibrosis and cirrhosis (possibly leading to chronic hepatic failure). The etiology of PNALD is multifactorial; however, intravenously administered phytosterols (plant sterols) contained in plant-derived lipid emulsions, such as Intralipid (included in PERIKABIVEN), have been associated with development of PNALD.

In a randomized study of neonates and infants expected to be treated with PN for at least 28 days, parenteral nutrition-associated cholestasis (PNAC), a precursor to PNALD, developed more frequently in Intralipid-treated patients than in patients treated with a 4-oil mixed lipid emulsion [see Adverse Reactions (6.1), Use in Specific Populations (8.4)].

Monitor liver tests in patients treated with PERIKABIVEN and consider discontinuation or dosage reduction if abnormalities occur.

Other Hepatobiliary Disorders

Hepatobiliary disorders including cholecystitis and cholelithiasis have developed in some PN-treated patients without preexisting liver disease.

Monitor liver tests when administering PERIKABIVEN. Patients developing signs of hepatobiliary disorders should be assessed early to determine whether these conditions are related to PERIKABIVEN use.

5.3 Pulmonary Embolism and Respiratory Distress due to Pulmonary Vascular Precipitates

Pulmonary vascular precipitates causing pulmonary emboli (including some fatalities) and respiratory distress have been reported in patients receiving parenteral nutrition.

Excessive addition of calcium and phosphate increases the risk of the formation of calcium phosphate precipitates; however, precipitates have been reported even in the absence of phosphate salt in the solution. Precipitation following passage through an in-line filter and suspected in vivo precipitate formation has also been reported.

Visually inspect the prepared solution, the infusion set, and catheter for precipitates, prior to administration as well as periodically during the administration. If signs of respiratory distress or pulmonary embolism occur, stop the PERIKABIVEN infusion and initiate a medical evaluation.

5.4 Hypersensitivity Reactions

PERIKABIVEN contains soybean oil, which may cause hypersensitivity reactions. Cross reactions have been observed between soybean and peanut. In postmarketing experience, anaphylaxis has been reported following Kabiven administration [see Adverse Reactions (6.2)].

PERIKABIVEN is contraindicated in patients with known hypersensitivity to egg, soybean, peanut or any of the active or inactive ingredients in PERIKABIVEN [see Contraindications (4)]. If a hypersensitivity reaction occurs, stop infusion of PERIKABIVEN immediately and initiate appropriate treatment and supportive measures.

5.5 Precipitation with Ceftriaxone

Precipitation of ceftriaxone-calcium can occur when ceftriaxone is mixed with calcium-containing parenteral nutrition solutions, such as PERIKABIVEN in the same intravenous administration line. Do not administer ceftriaxone simultaneously with PERIKABIVEN via a Y-site.

However, in patients other than neonates, ceftriaxone and PERIKABIVEN may be administered sequentially if the infusion lines are thoroughly flushed between infusions with a compatible fluid [see Dosage and Administration (2.1)].

Deaths have occurred in neonates (28 days of age or younger) who received concomitant intravenous calcium-containing solutions with ceftriaxone resulting from calcium-ceftriaxone precipitates in the lungs and kidneys, even when separate infusion lines were used [see Contraindications (4), Pediatric Use (8.4)].

5.6 Infections

Parenteral nutrition, such as PERIKABIVEN, can support microbial growth and is an independent risk factor for the development of catheter-related bloodstream infections. To decrease the risk of infectious complications, ensure aseptic techniques are used for catheter placement, catheter maintenance, and preparation and administration of PERIKABIVEN.

Monitor for signs and symptoms of infection including fever and chills, as well as laboratory test results that might indicate infection (including leukocytosis and hyperglycemia). Perform frequent checks of the intravenous catheter insertion site for edema, redness, and discharge.

5.7 Fat Overload Syndrome

Fat overload syndrome is a rare condition that has been reported with intravenous lipid formulations and is characterized by a sudden deterioration in the patient's condition (e.g., fever, anemia, leukopenia, thrombocytopenia, coagulation disorders, hyperlipidemia, hepatomegaly, deteriorating liver function, and central nervous system manifestations such as coma). A reduced or limited ability to metabolize lipids, accompanied by prolonged plasma clearance (resulting in higher lipid levels), may result in this syndrome. Although fat overload syndrome has been most frequently observed when the recommended lipid dose or infusion rate was exceeded, cases have also been described when the lipid formulation was administered according to instructions.

If signs or symptoms of fat overload syndrome occur, stop PERIKABIVEN. The syndrome is usually reversible when the infusion including the lipid emulsion is stopped.

5.8 Refeeding Syndrome

Administering PN to severely malnourished patients with parenteral nutrition may result in refeeding syndrome, characterized by the intracellular shift of potassium, phosphorus, and magnesium as patients become anabolic. Thiamine deficiency and fluid retention may also develop. To prevent these complications, closely monitor severely undernourished patients and slowly increase their nutrient intake.

5.9 Diabetes and Hyperglycemia

Administration of dextrose at a rate exceeding the patient's utilization rate may lead to hyperglycemia, hyperosmolar coma, and death. Monitor blood glucose levels and treat hyperglycemia to maintain optimal glucose levels while infusing PERIKABIVEN. Insulin may be administered or adjusted to maintain optimal blood glucose levels during PERIKABIVEN administration.

5.10 Hypertriglyceridemia

The use of PERIKABIVEN is contraindicated in patients with hypertriglyceridemia with serum triglyceride concentrations >1,000 mg/dL.

Patients with conditions such as inherited lipid disorders, obesity, diabetes mellitus, or metabolic syndromes have a higher risk of developing hypertriglyceridemia with the use of PERIKABIVEN. In addition, patients with hypertriglyceridemia may have worsening of their hypertriglyceridemia with administration of PERIKABIVEN. Excessive dextrose administration may further increase such risk.

Evaluate patients' capacity to eliminate and metabolize the infused lipid emulsion by measuring serum triglycerides before the start of infusion (baseline value), with each increase in dosage, and regularly throughout treatment. If triglyceride levels are above 400 mg/dL in adults, stop the PERIKABIVEN infusion and monitor serum triglyceride levels to avoid clinical consequences of hypertriglyceridemia such as pancreatitis.

To minimize the risk of new or worsening of hypertriglyceridemia, assess high-risk patients for their overall energy intake including other sources of lipid and dextrose, as well as concomitant drugs that may affect lipid and dextrose metabolism.

5.11 Vein Damage and Thrombosis

The infusion of hypertonic nutrient injections into a peripheral vein may result in vein irritation, vein damage, and/or thrombosis. PERIKABIVEN is indicated for peripheral administration, or may be infused into a central vein; however, peripheral catheters should not be used for solutions with osmolarity of ≥ 900 mOsm/L. The catheter should be removed as soon as possible if thrombophlebitis develops.

5.12 Electrolyte Imbalance and Fluid Overload in Patients with Decreased Renal Function

Patients with decreased renal function, including those with pre-renal azotemia, renal obstruction, or intrinsic renal disease, may be at increased risk of electrolyte and fluid volume imbalance when receiving PN, including PERIKABIVEN. In patients with decreased renal function with electrolyte imbalance or fluid overload, the PERIKABIVEN should be used with caution in patients with renal impairment. PERIKABIVEN dosage (e.g., fluid, protein, and electrolyte content) may require adjustment.

Monitor renal function parameters. Patients developing signs of decreased renal function should be assessed early by a clinician knowledgeable in renal disease in order to determine the appropriate PERIKABIVEN dosage and other treatment options.

5.13 Aluminum Toxicity

PERIKABIVEN contains no more than 25 mcg/L of aluminum.

The aluminum contained in PERIKABIVEN may reach toxic levels with prolonged parenteral administration in patients with impaired kidney function. Preterm infants are at greater risk because their kidneys are immature, and they require large amounts of calcium and phosphate solutions that contain aluminum. Patients with impaired kidney function, including preterm infants, who receive parenteral levels of aluminum at greater than 4 to 5 mcg/kg/day, accumulate aluminum at levels associated with central nervous system and bone toxicity. Tissue loading may occur at even lower rates of administration of total parenteral nutrition products.

5.14 Monitoring/Laboratory Tests

Monitor fluid status closely in patients with pulmonary edema or heart failure.

Throughout treatment, monitor serum triglycerides [see Warnings and Precautions (5.13)], fluid and electrolyte status, serum osmolarity, blood glucose, liver and kidney function, blood count (including platelets), and coagulation parameters.

PERIKABIVEN contains Vitamin K that may counteract anticoagulant activity [see Drug Interactions (7)].

The lipids contained in PERIKABIVEN may interfere with some laboratory tests (e.g., hemoglobin, triglycerides, lactate dehydrogenase, bilirubin, and oxygen saturation) if blood is sampled before the lipids in PERIKABIVEN have cleared from the bloodstream. Conduct these tests at least 6 hours after stopping the infusion.

6 ADVERSE REACTIONS

The following serious adverse reactions are discussed in greater detail in other sections of the prescribing information.

- Clinical Decompensation with Rapid Infusion of Intravenous Lipid Emulsion in Neonates and Infants [see Warnings and Precautions (5.1)].
- Parenteral Nutrition-Associated Liver Disease and Other Hepatobiliary Disorders [see Warnings and Precautions (5.2)].
- Pulmonary Embolism and Respiratory Distress due to Pulmonary Vascular Precipitates [see Warnings and Precautions (5.3)].
- Hypersensitivity Reactions [see Warnings and Precautions (5.4)].
- Precipitation with Ceftriaxone [see Warnings and Precautions (5.5)].
- Infections [see Warnings and Precautions (5.6)].
- Fat Overload Syndrome [see Warnings and Precautions (5.7)].
- Refeeding Syndrome [see Warnings and Precautions (5.8)].
- Diabetes and Hyperglycemia [see Warnings and Precautions (5.9)].
- Hypertriglyceridemia [see Warnings and Precautions (5.10)].
- Vein Damage and Thrombosis [see Warnings and Precautions (5.11)].
- Electrolyte Imbalance and Fluid Overload in Patients with Decreased Renal Function [see Warnings and Precautions (5.12)].
- Aluminum Toxicity [see Warnings and Precautions (5.13)].

6.1 Clinical Trials Experience

Because clinical trials are conducted under widely varying conditions, adverse reaction rates observed in the clinical trials of a drug cannot be directly compared to rates in the clinical trials of another drug and may not reflect the rates observed in practice.

The clinical data described for PERIKABIVEN reflects exposure in 93 patients exposed for 5 to 7 days in 4 active-controlled trials. The pooled population exposed to PERIKABIVEN was 18 to 87 years old, 48% female, 73% Caucasian. The enrolled patients had varied underlying conditions such as gastrointestinal disorders (55%), vascular disorders (30%), metabolism and nutrition disorders (28%), respiratory, thoracic, and mediastinal disorders (22%), and psychiatric disorders (20%). Most patients received peripheral intravenous infusion doses of ≥80% of their target mean daily exposure.

Adverse reactions occurring in at least 2% of patients who received PERIKABIVEN are shown in Table 3.

Table 3: Adverse Reactions in >2% of Patients Treated with PERIKABIVEN
Adverse reaction | PERIKABIVEN N=93 (%)
Hyperglycemia* | 5 (5)
Hypokalemia | 4 (4)
Pyrexia | 4 (4)
Blood triglycerides increased | 3 (3)
Phlebitis | 2 (2)
Nausea | 2 (2)
Pruritus | 2 (2)
Gamma-glutamyltransferase increased | 2 (2)
Blood alkaline phosphatase increased | 2 (2)
Alanine aminotransferase increased | 2 (2)
Blood glucose increased* | 2 (2)
C-reactive protein increased | 2 (2)
Blood urea increased | 2 (2)
Hypoalbuminemia | 2 (2)
* Terms as reported in clinical studies

Less common adverse reactions in ≤1% of patients who received PERIKABIVEN were hyperkalemia, hypomagnesaemia, hypernatremia, tachycardia, hypertension, thrombophlebitis, vomiting, jaundice, rash and increased blood bilirubin.

In a randomized active-controlled, double-blind, parallel-group, multi-center study that included 152 neonates and 9 patients ranging in age from 29 to 153 days who were expected to require PN for at least 28 days, parenteral nutrition-associated cholestasis (PNAC), a precursor to PNALD, developed more frequently in Intralipid-treated patients than in patients treated with a 4-oil mixed lipid emulsion. Intralipid is the lipid emulsion component of PERIKABIVEN.

PNAC (defined as direct bilirubin >2mg/dl with a second confirmed elevation >2mg/dl at least 7 days later) occurred in 11.5% (9/78) of Intralipid-treated patients and 2.4% (2/83) of patients treated with a 4-oil mixed lipid emulsion. Most PNAC events occurred in patients who were treated for longer than 28 days.

The estimated cumulative incidence of PNAC is shown in the Kaplan-Meier cumulative incidence curve in Figure 1.

Figure 1: Cumulative Incidence Curve of Time to Parenteral Nutrition-Associated Cholestasis (PNAC) with Standard Error Bars

Monitor liver tests in patients treated with PERIKABIVEN and consider discontinuation or dosage reduction if abnormalities occur.

6.2 Postmarketing Experience

The following additional adverse reactions have been identified during post-approval use of PERIKABIVEN in countries where it is registered. Because these reactions are reported voluntarily post-approval from a population of uncertain size, it is not always possible to reliably estimate their frequency or establish a causal relationship to product exposure.

- Gastrointestinal disorders: abdominal distension, abdominal pain
- General disorders and administration site conditions: chest tightness
- Hepatobiliary disorders: cholestasis
- Immune system disorders: hypersensitivity reactions including anaphylaxis [see Contraindications (4), Warnings and Precautions (5.4)]
- Infections and infestations: infection
- Vascular disorders: flushed face

7 DRUG INTERACTIONS

7.1 Ceftriaxone

Precipitation of ceftriaxone-calcium can occur when ceftriaxone is mixed with calcium-containing parenteral nutrition solutions, such as PERIKABIVEN, in the same intravenous administration line. Do not administer ceftriaxone simultaneously with PERIKABIVEN, via a Y-site. However, ceftriaxone and PERIKABIVEN, may be administered sequentially if the infusion lines are thoroughly flushed between infusions with a compatible fluid [see Dosage and Administration (2.1)].

Deaths have occurred in neonates (28 days of age or younger) who received concomitant intravenous calcium-containing solutions with ceftriaxone resulting from calcium-ceftriaxone precipitates in the lungs and kidneys, even when separate infusion lines were used [see Contraindications (4), Use in Specific Populations (8.4)].

7.2 Coumarin and Coumarin Derivatives

The soybean oil present in PERIKABIVEN has vitamin K1. Vitamin K1 can reverse the anticoagulant activity of coumarin or coumarin derivatives, which work by blocking recycling of vitamin K1. Monitoring for anticoagulant activity is recommended in patients who are on both PERIKABIVEN and coumarin or coumarin derivatives.

8 USE IN SPECIFIC POPULATIONS

8.1 Pregnancy

Risk Summary

The limited available data on the use of PERIKABIVEN in pregnant women are not sufficient to inform a drug-associated risk. However, there are clinical considerations if PERIKABIVEN is used in pregnant women [see Clinical Considerations]. Animal reproduction studies have not been conducted with PERIKABIVEN.

The estimated background risk of major birth defects and miscarriage for the indicated population are unknown. In the U.S. general population, the estimated background risk of major birth defects and miscarriage in clinically recognized pregnancies is 2 to 4% and 15 to 20%, respectively.

Clinical Considerations

Disease-Associated Maternal and/or Embryofetal Risk

Severe malnutrition in a pregnant woman is associated with preterm delivery, low birth weight, intrauterine growth restriction, congenital malformations and perinatal mortality. Parenteral nutrition should be considered if a pregnant woman's nutritional requirements cannot be fulfilled by oral or enteral intake.

8.2 Lactation

Risk Summary

There are no data available to assess the presence of PERIKABIVEN and/or its active metabolite(s) in human milk, the effects on the breastfed child or the effects on milk production. The developmental and health benefits of breastfeeding should be considered along with the mother's clinical need for PERIKABIVEN, and any potential adverse effects of PERIKABIVEN on the breastfed child or from the underlying maternal condition.

8.4 Pediatric Use

The safety and effectiveness of PERIKABIVEN has not been established in pediatric patients of any age. In the postmarketing setting, clinical decompensation with rapid infusion of intravenous lipid emulsion in neonates and infants, sometimes fatal has been reported [see Warnings and Precautions (5.1)]. Patients, particularly preterm infants, are at risk for aluminum toxicity [see Warnings and Precautions (5.13)].

Deaths have occurred in neonates (28 days of age or younger) who received concomitant intravenous calcium-containing solutions with ceftriaxone resulting from calcium-ceftriaxone precipitates in the lungs and kidneys, even when separate infusion lines were used. [see Contraindications (4), Warnings and Precautions (5.5)].

PERIKABIVEN is not recommended for use in pediatric patients under the age of two years, including preterm infants, as the fixed content of the formulation does not meet the nutritional requirements of this age group due to the following reasons:

- Calcium and dextrose needs are not met and lipids, protein and magnesium exceed requirements.
- The product does not contain the amino acids cysteine and taurine, considered conditionally essential for neonates and infants.

Patients, including pediatric patients, may be at risk for PNALD [see Warnings and Precautions (5.2)].

Newborns – especially those born premature and with low birth weight – are at increased risk of developing hypo – or hyperglycemia and therefore need close monitoring during treatment with intravenous dextrose solutions to ensure adequate glycemic control in order to avoid potential long term adverse effects. Hypoglycemia in the newborn can cause prolonged seizures, coma and brain damage. Hyperglycemia has been associated with intraventricular hemorrhage, late onset bacterial and fungal infection, retinopathy of prematurity, necrotizing enterocolitis, bronchopulmonary dysplasia, prolonged length of hospital stay, and death.

8.5 Geriatric Use

Clinical studies of PERIKABIVEN did not include sufficient numbers of patients aged 65 and over to determine whether they respond differently from other younger patients. Other reported clinical experience has not identified differences in responses between the elderly and younger patients. In general, dose selection for an elderly patient should be cautious, usually starting at the low end of the dosing range, reflecting the greater frequency of decreased hepatic, renal, or cardiac function, and of concomitant disease or drug therapy.

10 OVERDOSAGE

In the event of overdose, serious adverse reactions may result [see Warnings and Precautions (5.1, 5.7)]. Stop the infusion of PERIKABIVEN to allow lipids to clear from serum. The effects are usually reversible after the lipid infusion is stopped. If medically appropriate, further intervention may be indicated. The lipid administered and fatty acids produced are not dialyzable.

11 DESCRIPTION

PERIKABIVEN is a sterile, hypertonic emulsion, for peripheral or central venous administration, in a Three Chamber Bag. The product contains no added sulfites.

Chamber 1 contains Dextrose monohydrate solution for fluid replenishment and caloric supply.

Chamber 2 contains the Amino Acid solution with Electrolytes, which comprises essential and nonessential amino acids provided with electrolytes.

Chamber 3 contains Intralipid® 20% (a 20% Lipid Injectable Emulsion), prepared for intravenous administration as a source of calories and essential fatty acids.

See below for formulations of each chamber and Table 2 for strength, pH, osmolarity, ionic concentration and caloric content of PERIKABIVEN when all the chambers are mixed together.

Chamber 1: Contains sterile, hypertonic solution of Dextrose, USP in water for injection with a pH range of 3.5 to 5.5. Dextrose, USP is chemically designated D-glucose, monohydrate (C6H12O6 • H2O) and has the following structure:

Dextrose is derived from corn.

Chamber 2: Contains a sterile solution of amino acids and electrolytes in water for injection. In addition, glacial acetic acid has been added to adjust the pH so that the final solution pH is 5.4 to 5.8. The formulas for the individual electrolytes and amino acids are as follows:

Electrolytes
Sodium Acetate Trihydrate, USP | CH3COONax3H2O
Potassium Chloride, USP | KCl
Sodium Glycerophosphate | C3H5(OH)2PO4Na2xH2O
Magnesium Sulfate Heptahydrate, USP | MgSO4x7H2O
Calcium Chloride Dihydrate, USP | CaCl2x2H2O
Essential Amino Acids
Lysine (added as the hydrochloride salt) | H2N(CH2)4CH(NH2)COOH.HCl
Phenylalanine | CH2CH(NH2)COOH
Leucine | (CH3)2CHCH2CH(NH2)COOH
Valine | (CH3)2CHCH(NH2)COOH
Histidine | CH2CH(NH2)COOH
Threonine | CH3CH(OH)CH(NH2)COOH
Methionine | CH3S(CH2)2CH(NH2)COOH
Isoleucine | CH3CH2CH(CH3)CH(NH2)COOH
Tryptophan | CH2CH(NH2)COOH
Nonessential Amino Acids
Alanine | CH3CH(NH2)COOH
Arginine | H2NC(NH)NH(CH2)3CH(NH2)COOH
Glycine | H2NCH2COOH
Proline
Glutamic Acid | HOOC(CH2)2CH(NH2)COOH
Serine | HOCH2CH(NH2)COOH
Aspartic Acid | HOOCCH2CH(NH2)COOH
Tyrosine

Chamber 3: Contains a 20% Lipid Injectable Emulsion (Intralipid® 20%) which is made up of 20% Soybean Oil, 1.2% Egg Yolk Phospholipids, 2.25% Glycerin, and water for injection. In addition, sodium hydroxide has been added to adjust the pH. The final product pH range is 6 to 9.

The soybean oil is a refined natural product consisting of a mixture of neutral triglycerides of predominantly unsaturated fatty acids with the following structure:

where are saturated and unsaturated fatty acid residues. The major component fatty acids are linoleic (48 to 58 %), oleic (17 to 30%), palmitic (9 to 13%), linolenic (5 to 11%) and stearic acid (2.5 to 5%). These fatty acids have the following chemical and structural formulas:

Linoleic acid
C18H32O2

Oleic acid
C18H34O2

Palmitic acid
C16H32O2

Linolenic acid
C18H30O2

Stearic acid
C18H36O2

Purified egg phosphatides are a mixture of naturally occurring phospholipids which are isolated from the egg yolk. These phospholipids have the following general structure:

contain saturated and unsaturated fatty acids that abound in neutral fats. R3 is primarily either the choline or ethanolamine ester of phosphoric acid.

Glycerin is chemically designated C3H8O3 and is a clear colorless, hygroscopic syrupy liquid. It has the following structural formula:

The container-solution unit is a closed system and is not dependent upon entry of external air during administration. The container is overwrapped to provide protection from the physical environment and to provide an additional oxygen and moisture barrier when necessary. An oxygen absorber is placed between the inner bag and the overpouch.

The container is not made with natural rubber latex or polyvinyl chloride (PVC). PERIKABIVEN contains no more than 25 mcg/L of aluminum.

12 CLINICAL PHARMACOLOGY

12.1 Mechanism of Action

PERIKABIVEN is used as a supplement or as the sole source of nutrition in patients, providing macronutrients (amino acids, dextrose and lipids) and micronutrients (electrolytes) parenterally.

The amino acids provide the structural units that make up proteins and are used to synthesize proteins and other biomolecules or are oxidized to urea and carbon dioxide as a source of energy.

The administered dextrose is oxidized to carbon dioxide and water, yielding energy.

Intravenously administered lipids provide a biologically utilizable source of calories and essential fatty acids. Fatty acids serve as an important substrate for energy production. The most common mechanism of action for energy derived from fatty acid metabolism is beta- oxidation. Fatty acids are important for membrane structure and function, precursors for bioactive molecules (such as prostaglandins), and as regulators of gene expression.

12.3 Pharmacokinetics

The infused lipid particles provided by PERIKABIVEN are expected to be cleared from the blood stream in a manner thought to be comparable to the clearing of chylomicrons. In healthy volunteers, the maximum clearance rate of the triglycerides after fasting overnight has been found to be 3.8 ± 1.5g/kg per 24 hours.

Both elimination and oxidation rates are dependent on the patient's clinical condition; elimination is faster and utilization is increased in postoperative patients, in sepsis, burns and trauma, while patients with renal impairment and hypertriglyceridemia may show lower utilization of exogenous lipid emulsions. Due to differences in elimination, patients with these conditions should be closely monitored during PERIKABIVEN administration [see Warnings and Precautions (5.10, 5.12)].

The disposition of infused amino acids, dextrose and electrolytes are essentially the same as those supplied by ordinary food.

A clinical study in healthy volunteers employing high intravenous doses (80 mmol) of either sodium glycerophosphate used in PERIKABIVEN or reference, inorganic sodium phosphate demonstrated that both compounds resulted in comparable serum inorganic phosphate concentrations after a single intravenous dose. Changes from baseline in the serum levels of sodium, potassium and total calcium were comparable across the two phosphate sources in this study.

13 NONCLINICAL TOXICOLOGY

13.1 Carcinogenesis, Mutagenesis, Impairment of Fertility

Long-term animal studies have not been conducted to evaluate carcinogenic potential of PERIKABIVEN or its effect on fertility. Genotoxicity studies have not been conducted with PERIKABIVEN to assess its mutagenic potential.

16 HOW SUPPLIED/STORAGE AND HANDLING

PERIKABIVEN is a sterile emulsion available in the following 2 sizes:

NDC | Volume
63323-714-19 | 1,920 mL
63323-714-14 | 1,440 mL

Exposure of pharmaceutical products to heat should be minimized. Avoid excessive heat. Protect from freezing. If accidentally frozen, discard the bag. It is recommended that the product be stored at 5°C to 25°C (41°F to 77°F).

Do not remove container from overpouch until intended for use.

After breaking the vertical seals, chemical and physical in-use stability of the mixed three chamber bag has been demonstrated for 24 hours at 25°C (77°F).

The product should be used immediately after the introduction of additives. If not used immediately, the storage time and conditions prior to use should not be longer than 24 hours at 2° to 8°C (36° to 46°F). After removal from storage at 2° to 8°C (36° to 46°F), the admixture should be infused within 24 hours. Any mixture remaining must be discarded.

17 PATIENT COUNSELING INFORMATION

When initiating PERIKABIVEN administration, discuss the following information with the patient or caregiver:

Parenteral Nutrition-Associated Liver Disease and Other Hepatobiliary Disorders

Inform patients and caregivers that use of parenteral nutrition may result in parenteral nutrition- associated liver disease and/or other hepatobiliary disorders [see Warnings and Precautions (5.2)].

Pulmonary Embolism and Respiratory Distress due to Pulmonary Vascular Precipitates

Inform patients and caregivers that pulmonary vascular precipitates causing pulmonary emboli (including some fatalities) and presenting as respiratory distress have been reported in patients receiving parenteral nutrition. If PERIKABIVEN is infused at home, instruct patients or caregivers to visually inspect the prepared solution, the infusion set, and catheter for precipitates, prior to administration as well as periodically during the administration [see Warnings and Precautions (5.3)]

Hypersensitivity Reactions

Inform patients and caregivers that PERIKABIVEN may cause hypersensitivity reactions, including anaphylaxis. If PERIKABIVEN is infused at home, instruct patients or caregivers to stop the infusion of PERIKABIVEN immediately and seek medical attention if they experience signs or symptoms of a hypersensitivity reaction, such as rapid or weak heartbeat, feeling faint, difficulty in breathing or swallowing, vomiting, nausea, headache, sweating, dizziness, hives, rash, itching, flushing, dizziness, fever, or chills [see Warnings and Precautions (5.4)].

Infections

Inform patients and caregivers that patients who receive PERIKABIVEN are at risk of infection. If PERIKABIVEN is infused at home, instruct patients or caregivers to ensure aseptic techniques are used for the preparation and administration of PERIKABIVEN and to monitor for signs and symptoms of infection [see Warnings and Precautions (5.6)].

Fat Overload Syndrome

Inform patients and caregivers that fat overload syndrome has been reported with the use of intravenous lipid emulsions. If PERIKABIVEN is infused at home, instruct patients or caregivers to stop PERIKABIVEN if signs or symptoms of fat overload syndrome occur [see Warnings and Precautions (5.7)].

Refeeding Syndrome

If the patient is severely malnourished, inform patients and caregivers that administering parenteral nutrition including PERIKABIVEN may result in refeeding syndrome [see Warnings and Precautions (5.8)].

Diabetes and Hyperglycemia

Inform patients and their caregivers that administration of dextrose at a rate exceeding the patient's utilization rate may lead to hyperglycemia, hyperosmolar coma, and death [see Warnings and Precautions (5.9)].

Hypertriglyceridemia

Inform patients and their caregivers about the risks of hypertriglyceridemia with PERIKABIVEN use [see Warnings and Precautions (5.10)].

Vein Damage and Thrombosis

Inform patients and caregivers that the infusion of hypertonic nutrient injections into a peripheral vein may result in vein irritation, vein damage, and/or thrombosis [see Warnings and Precautions (5.11)].

Electrolyte Imbalance and Fluid Overload in Patients with Decreased Renal Function

For patients with decreased renal function, inform them or their caregivers that the patient may be at increased risk of electrolyte and fluid volume imbalance when PERIKABIVEN is being administered [see Warnings and Precautions (5.12)].

Aluminum Toxicity

Inform patients and their caregivers that prolonged PN administration in patients with renal impairment, including preterm neonates, may result in aluminum reaching toxic levels associated with central nervous system and bone toxicity [see Warnings and Precautions (5.13)].

Preparation and Administration Instructions

If it is acceptable for a patient or caregiver to administer PERIKABIVEN at home, then the patient or caregiver must be trained on the following: how to inspect and prepare, add compatible additives (when appropriate), administer, and store PERIKABIVEN [see Dosage and Administration (2.1, 2.2)]. Inform patients or caregivers not to deviate from the administration instructions given by the healthcare provider.

Manufactured by:

Uppsala, Sweden

Fresenius Kabi, Perikabiven and Intralipid are registered trademarks of Fresenius Kabi. U.S. Patents 12213943 and 12390398.

www.freseniuskabinutrition.com/products/kabiven-perikabiven/

451207G

PACKAGE LABEL

PACKAGE LABEL - PRINCIPAL DISPLAY PANEL - PERIKABIVEN ®1440 mL Bag Label

PERIKABIVEN ® 1440 mL

Amino Acids, Electrolytes, Dextrose, and Lipid Injectable Emulsion, for intravenous use

(2.4%, 0.5%*, 7.5% and 3.5%), No sulfites added PERIPHERAL INFUSION

PACKAGE LABEL

PACKAGE LABEL - PRINCIPAL DISPLAY PANEL - PERIKABIVEN ®1440 mL Bag Shipper Label

NDC 63323-714-14

PERIKABIVEN ® 4 x 1440 mL

Amino Acids, Electrolytes, Dextrose, and Lipid Injectable Emulsion, for intravenous use

(2.4%, 0.5%*, 7.5% and 3.5%),

No sulfites added PERIPHERAL INFUSION

Rx only

PACKAGE LABEL

PACKAGE LABEL - PRINCIPAL DISPLAY PANEL - PERIKABIVEN ®1920 mL Bag Label

PERIKABIVEN ® 1920 mL

Amino Acids, Electrolytes, Dextrose, and Lipid Injectable Emulsion, for intravenous use

(2.4%, 0.5%*, 7.5% and 3.5%), No sulfites added PERIPHERAL INFUSION

PACKAGE LABEL

PACKAGE LABEL - PRINCIPAL DISPLAY PANEL - PERIKABIVEN ®1920 mL Bag Shipper Label

NDC 63323-714-19

PERIKABIVEN ® 4 x 1920 mL

Amino Acids, Electrolytes, Dextrose, and Lipid Injectable Emulsion, for intravenous use

(2.4%, 0.5%*, 7.5% and 3.5%),

No sulfites added PERIPHERAL INFUSION

Rx only